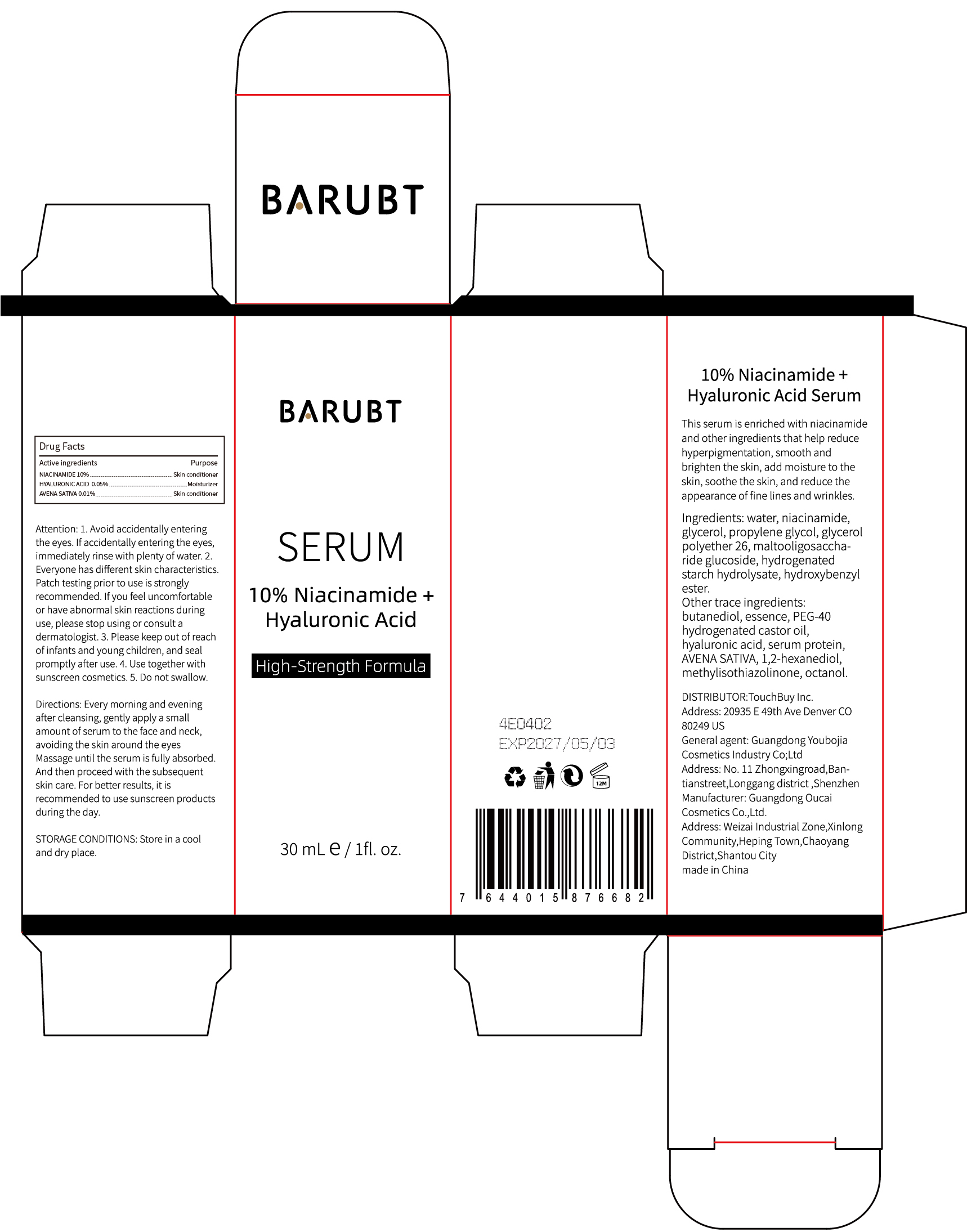 DRUG LABEL: BARUBT Niacinamide Hyaluronic Acid Serum
NDC: 84712-009 | Form: LOTION
Manufacturer: Guangdong Youbaijia Cosmetic Industry Co., Ltd
Category: otc | Type: HUMAN OTC DRUG LABEL
Date: 20240913

ACTIVE INGREDIENTS: AVENA SATIVA WHOLE 0.003 g/30 mL; NIACINAMIDE 3 g/30 mL; HYALURONIC ACID 0.015 g/30 mL
INACTIVE INGREDIENTS: 1,2-HEXANEDIOL 0.015 g/30 mL; HYDROGENATED STARCH HYDROLYSATE 0.003 g/30 mL

ACTIVE INGREDIENT

niacinamide 10%
hyaluronic acid 0.05%
AVENA SATIVA 0.01%

INACTIVE INGREDIENT

water
glycerol
propylene glycol
glycerol polyether 26
maltooligosaccharide glucoside
hydrogenated starch hydrolysate
hydroxybenzyl ester
butanediol
essence
PEG-40 hydrogenated castor oil
serum protein
1,2-hexanediol
methylisothiazolinone
octanol

DO NOT USE

on damaged or broken skin

PURPOSE

reduce the appearance of fine lines and wrinkles.

Keep away from children. Do not swallow.

STOP USE

if you feel uncomfortable or have abnormal skin reactions during use, please stop using or consult a dermatologist.

WHEN USING

Avoid accidentally entering the eyes. If accidentally entering the eyes, immediately rinse with plenty of water.

DOSAGE AND ADMINISTRATION

Every morning and evening after cleansing, gently apply a small amount of serum to the face and neck, avoiding the skin around the eyes
Massage until the serum is fully absorbed. And then proceed with the subsequent skin care. For better results, it is recommended to use sunscreen products during the day.

QUESTIONS

Contact name: Jessie Peng
Company phone number: +1 818 579 7288
Company e-mail: jessie@registeragentllc.com

WARNINGS

For external use only.

INDICATIONS AND USAGE

This serum is enriched with niacinamide and other ingredients that help reduce hyperpigmentation,smooth and brighten the skin, add moisture to the skin, soothe the skin, and reduce the appearance of fine lines and wrinkles.

STORAGE AND HANDLING

Store in a cool and dry place.